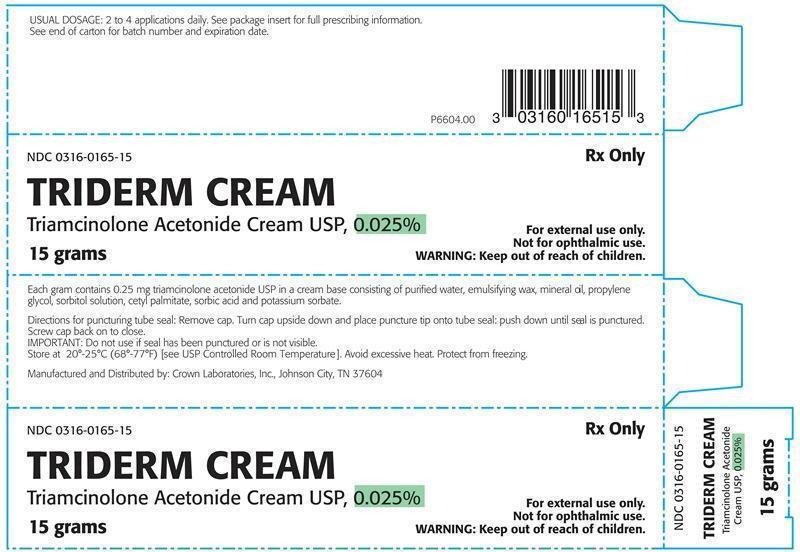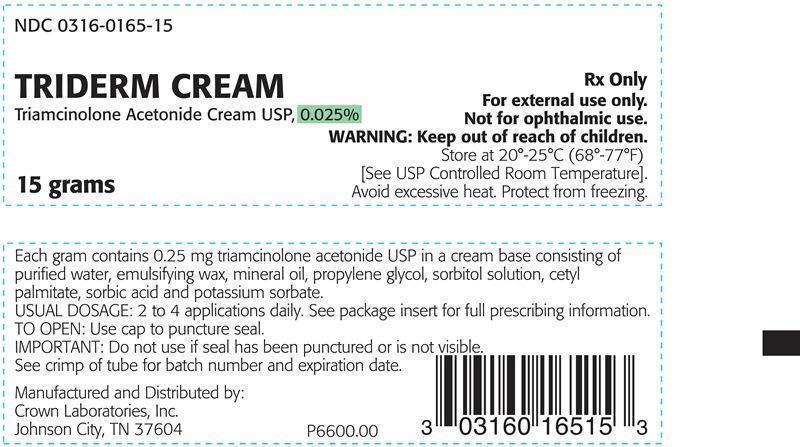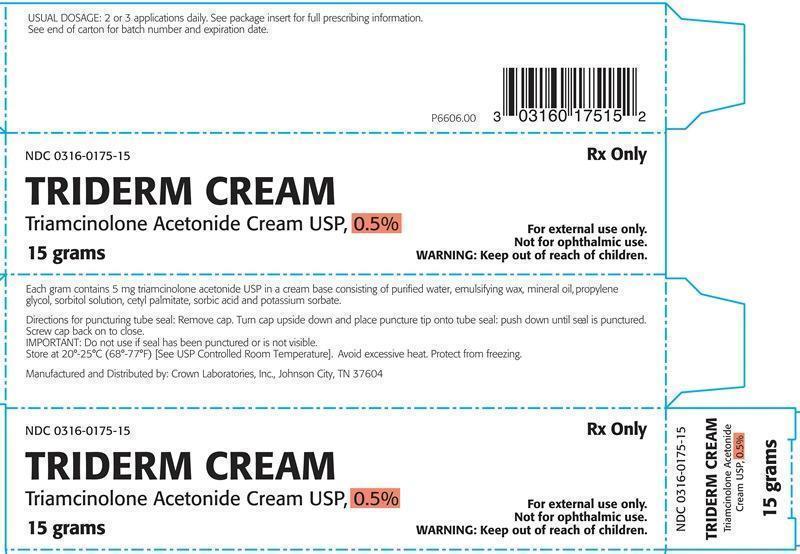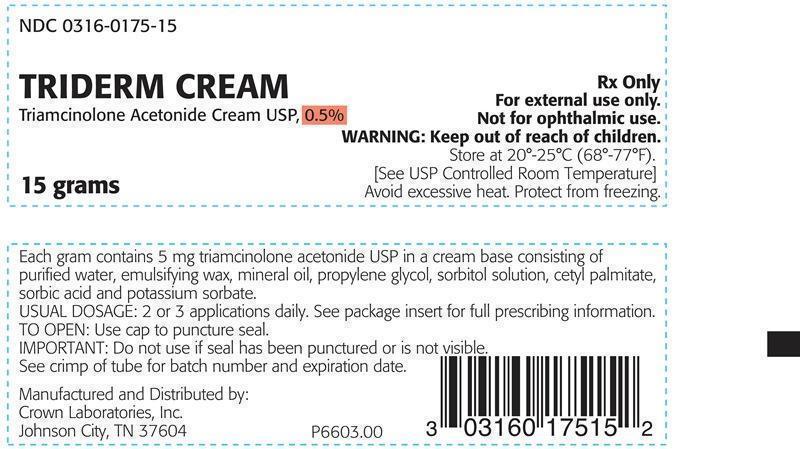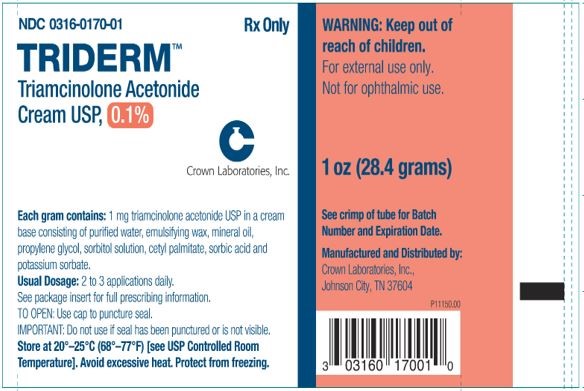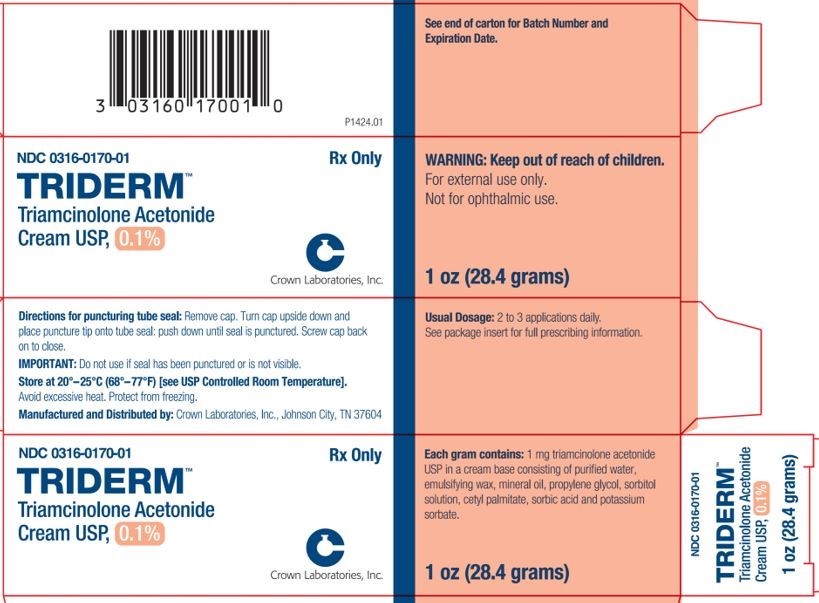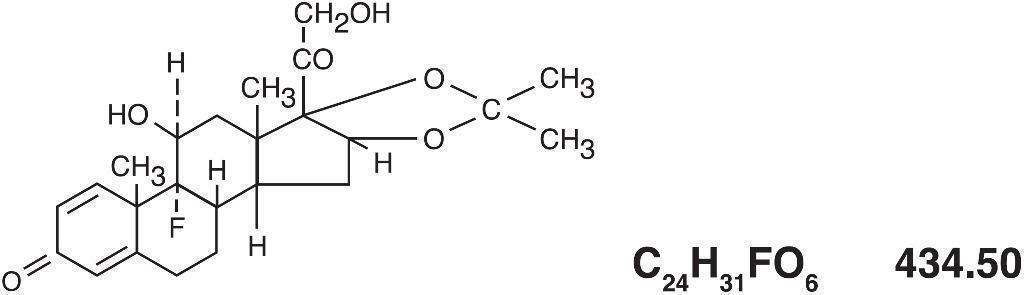 DRUG LABEL: TRIDERM
NDC: 0316-0175 | Form: CREAM
Manufacturer: Crown Laboratories
Category: prescription | Type: HUMAN PRESCRIPTION DRUG LABEL
Date: 20260112

ACTIVE INGREDIENTS: TRIAMCINOLONE ACETONIDE 5 mg/1 g
INACTIVE INGREDIENTS: SORBITOL; POTASSIUM SORBATE; WATER; CETYL PALMITATE; SORBIC ACID; PROPYLENE GLYCOL; MINERAL OIL; POLAWAX POLYSORBATE

TRIDERM (Triamcinolone Acetonide Cream USP), 0.025%, 0.1%, 0.5%

DESCRIPTION

The topical corticosteroids constitute a class of primarily synthetic steroids used as anti-inflammatory and antipruritic agents. Triamcinolone acetonide is a member of this class. Triamcinolone acetonide is chemically pregna-1,4-diene-3,20-dione, 9-fluoro-11,21-dihydroxy-16,17-[(1-methylethylidene)bis-(oxy)]-(11β, 16α)- with the empirical formula C24H31FO6 and molecular weight 434.50. Its structural formula is:

Each gram of Triderm (Triamcinolone Acetonide Cream USP), 0.025% contains 0.25 mg triamcinolone acetonide USP in a cream base consisting of purified water, emulsifying wax, mineral oil, propylene glycol, sorbitol solution, cetyl palmitate, sorbic acid, and potassium sorbate.

Each gram of Triderm (Triamcinolone Acetonide Cream USP), 0.1% contains 1 mg triamcinolone acetonide USP in a cream base consisting of purified water, emulsifying wax, mineral oil, propylene glycol, sorbitol solution, cetyl palmitate, sorbic acid, and potassium sorbate.

Each gram of Triderm (Triamcinolone Acetonide Cream USP), 0.5% contains 5 mg triamcinolone acetonide USP in a cream base consisting of purified water, emulsifying wax, mineral oil, propylene glycol, sorbitol solution, cetyl palmitate, sorbic acid, and potassium sorbate.

CLINICAL PHARMACOLOGY

Topical corticosteroids share anti-inflammatory, antipruritic and vasoconstrictive actions.
The mechanism of anti-inflammatory activity of the topical corticosteroids is unclear. Various laboratory methods, including vasoconstrictor assays, are used to compare and predict potencies and/or clinical efficacies of the topical corticosteroids. There is some evidence to suggest that a recognizable correlation exists between vasoconstrictor potency and therapeutic efficacy in man.

Pharmacokinetics
The extent of percutaneous absorption of topical corticosteroids is determined by many factors including the vehicle, the integrity of the epidermal barrier, and the use of occlusive dressings.
Topical corticosteroids can be absorbed from normal intact skin. Inflammation and/or other disease processes in the skin increase percutaneous absorption. Occlusive dressings substantially increase the percutaneous absorption of topical corticosteroids. Thus, occlusive dressings may be a valuable therapeutic adjunct for treatment of resistant dermatoses. (See DOSAGE AND ADMINISTRATION).
Once absorbed through the skin, topical corticosteroids are handled through pharmacokinetic pathways similar to systemically administered corticosteroids. Corticosteroids are bound to plasma proteins in varying degrees. Corticosteroids are metabolized primarily in the liver and are then excreted by the kidneys. Some of the topical corticosteroids and their metabolites are also excreted into the bile.

INDICATIONS AND USAGE

Topical corticosteroids are indicated for the relief of the inflammatory and pruritic manifestations of corticosteroid-responsive dermatoses.

CONTRAINDICATIONS

Topical corticosteroids are contraindicated in those patients with a history of hypersensitivity to any of the components of the preparation.

PRECAUTIONS

General
Systemic absorption of topical corticosteroids has produced reversible hypothalamic-pituitary-adrenal (HPA) axis suppression, manifestations of Cushing’s syndrome, hyperglycemia, and glucosuria in some patients.
Conditions which augment systemic absorption include the application of the more potent steroids, use over large surface areas, prolonged use, and the addition of occlusive dressings.
Therefore, patients receiving a large dose of a potent topical steroid applied to a large surface area or under an occlusive dressing should be evaluated periodically for evidence of HPA axis suppression by using the urinary free cortisol and ACTH stimulation tests. If HPA axis suppression is noted, an attempt should be made to withdraw the drug, to reduce the frequency of application, or to substitute a less potent steroid.
Recovery of HPA axis function is generally prompt and complete upon discontinuation of the drug. Infrequently, signs and symptoms of steroid withdrawal may occur, requiring supplemental systemic corticosteroids. Pediatric patients may absorb proportionally larger amounts of topical corticosteroids and thus be more susceptible to systemic toxicity (See PRECAUTIONS-Pediatric use).
If irritation develops, topical corticosteroids should be discontinued and appropriate therapy instituted.
In the presence of dermatological infections, the use of an appropriate antifungal or antibacterial agent should be instituted. If a favorable response does not occur promptly, the corticosteroid should be discontinued until the infection has been adequately controlled.

Information for the Patient

Patients using topical corticosteroids should receive the following information and instructions:
1. This medication is to be used as directed by the physician. It is for external use only. Avoid contact with the eyes.
2. Patients should be advised not to use this medication for any disorder other than for which it was prescribed.
3. The treated skin area should not be bandaged or otherwise covered or wrapped as to be occlusive unless directed by the physician.
4. Patients should report any signs of local adverse reactions especially under occlusive dressing.
5. Parents of pediatric patients should be advised not to use tight-fitting diapers or plastic pants on a child being treated in the diaper area, as these garments may constitute occlusive dressings.

Laboratory Tests

The following tests may be helpful in evaluating the HPA axis suppression:
Urinary free cortisol test
ACTH stimulation test

Carcinogenesis, Mutagenesis, and Impairment of Fertility

Long-term animal studies have not been performed to evaluate the carcinogenic potential or the effect on fertility of topical corticosteroids.
Studies to determine mutagenicity with prednisolone and hydrocortisone have revealed negative results.

Pregnancy Category C

Corticosteroids are generally teratogenic in laboratory animals when administered systemically at relatively low dosage levels. The more potent corticosteroids have been shown to be teratogenic after dermal application in laboratory animals. There are no adequate and well-controlled studies in pregnant women on teratogenic effects from topically applied corticosteroids. Therefore, topical corticosteroids should be used during pregnancy only if the potential benefit justifies the potential risk to the fetus. Drugs of this class should not be used extensively on pregnant patients, in large amounts, or for prolonged periods of time.

Nursing Mothers

It is not known whether topical administration of corticosteroids could result in sufficient systemic absorption to produce detectable quantities in breast milk. Systemically administered corticosteroids are secreted into breast milk in quantities not likely to have a deleterious effect on the infant. Nevertheless, caution should be exercised when topical corticosteroids are administered to a nursing woman.

Pediatric Use

Pediatric patients may demonstrate greater susceptibility to topical corticosteroid-induced HPA axis suppression and Cushing’s syndrome than mature patients because of a larger skin surface area to body weight ratio.
Hypothalamic-pituitary-adrenaI (HPA) axis suppression, Cushing’s syndrome, and intracranial hypertension have been reported in pediatric patients receiving topical corticosteroids. Manifestations of adrenal suppression in pediatric patients include linear growth retardation, delayed weight gain, low plasma cortisol levels, and absence of response to ACTH stimulation. Manifestations of intracranial hypertension include bulging fontanelles, headaches, and bilateral papilledema.
Administration of topical corticosteroids to pediatric patients should be limited to the least amount compatible with an effective therapeutic regimen. Chronic corticosteroid therapy may interfere with the growth and development of pediatric patients.

ADVERSE REACTIONS

The following local adverse reactions are reported infrequently with topical corticosteroids, but may occur more frequently with the use of occlusive dressings. These reactions are listed in an approximate decreasing order of occurrence: burning, itching, irritation, dryness, folliculitis, hypertrichosis, acneiform eruptions, hypopigmentation, perioral dermatitis, allergic contact dermatitis, maceration of the skin, secondary infection, skin atrophy, striae, miliaria.

OVERDOSAGE

Topically applied corticosteroids can be absorbed in sufficient amounts to produce systemic effects. (See PRECAUTIONS)

DOSAGE AND ADMINISTRATION

Apply to the affected area as a thin film from two to four times daily for the 0.025% strength and two or three times daily for the 0.1% and 0.5% strength depending on the severity of the condition.
Occlusive dressings may be used for the management of psoriasis or recalcitrant conditions.
If an infection develops, the use of occlusive dressings should be discontinued and appropriate antimicrobial therapy instituted.

HOW SUPPLIED

Triderm (Triamcinolone Acetonide Cream USP), 0.025% is supplied in:

15 grams tube NDC 0316-0165-15

85.2 grams tube NDC 0316-0165-85

454 grams jar NDC 0316-0165-16

Triderm (Triamcinolone Acetonide Cream USP), 0.1% is supplied in:
28.4 grams tube NDC 0316-0170-01

85.2 grams tube NDC 0316-0170-03

Triderm (Triamcinolone Acetonide Cream USP), 0.5% is supplied in:

15 grams tube NDC 0316-0175-15

454 grams jar NDC 0316-0175-16

STORAGE

Store at room temperature 20o - 25oC (68o- 77oF) [see USP Controlled Room Temperature]

Manufactured and Distributed by:

Crown Laboratories, Inc.

Johnson City, TN 37604

Revised: Sep 2017

PRINTED IN USA
P8002.03

Triderm (Triamcinolone Acetonide Cream USP), 0.1% tube label

NDC 0316-0170-01

Rx Only

TRIDERMTM

Triamcinolone Acetonide Cream USP, 0.1%

1 oz (28.4 grams)

WARNING: Keep Out Of Reach Of Children.

For external use only.

Not for ophthalmic use.

.

Each gram contains: 1 mg Triamcinolone Acetonide USP in a cream base consisting of purified water, emulsifying wax, mineral oil, propylene glycol, sorbitol solution, cetyl palmitate, sorbic acid, and potassium sorbate.

Usual Dosage: 2 to 3 applications daily. See package insert for full prescribing information.

TO OPEN: Use cap to puncture seal.

IMPORTANT: Do not use if seal has been punctured or is not visible.

Store at 20o-25oC (68o-77oF) [see USP Controlled Room Temperature]. Avoid excessive heat. Protect from freezing.

See Crimp of tube for Expiration Date and Batch Number.

Manufactured and Distributed by:

Crown Laboratories, Inc., Johnson City, TN 37604

Triderm (Triamcinolone Acetonide Cream USP), 0.1% carton label

NDC 0316-0170-01

Rx Only

TRIDERMTM
Triamcinolone Acetonide Cream USP, 0.1%

1 oz (28.4 grams)

WARNING: Keep Out Of Reach Of Children.

For External Use Only.
Not for Ophthalmic Use.

Each gram contains: 1 mg triamcinolone acetonide USP in a cream base consisting of purified water, emulsifying wax, mineral oil, propylene glycol, sorbitol solution, cetyl palmitate, sorbic acid, and potassium sorbate.

Directions for puncturing tube seal: Remove cap. Turn cap upside down and place puncture tip onto tube seal: push down until seal is punctured. Screw cap back on to close.

IMPORTANT: Do not use if seal has been punctured or is not visible.

Store at 20o-25oC (68o-77oF) [see USP Controlled Room Temperature].

Avoid excessive heat. Protect from freezing.

Manufactured and Distributed by: Crown Laboratories, Inc. Johnson City, TN 37604

Usual Dosage: 2 to 3 applications daily. See package insert for full prescribing information.

See end of carton for batch number and expiration date.

Triderm (Triamcinolone Acetonide Cream USP), 0.025% tube label

NDC 0316-0165-15

Rx Only

TRIDERM CREAMTM

Triamcinolone Acetonide Cream USP, 0.025%

15 grams

WARNING: Keep out of reach of children

For External Use Only
Not for Ophthalmic Use

Store at 20o-25oC (68o-77oF) [see USP Controlled Room Temperature]

Avoid excessive heat. Protect from freezing.

Each gram contains 0.25 mg triamcinolone acetonide USP in a cream base consisting of purified water, emulsifying wax, mineral oil, propylene glycol, sorbitol solution, cetyl palmitate, sorbic acid, and potassium sorbate.

USUAL DOSAGE: 2 or 4 applications daily. See package insert for full prescribing information.

TO OPEN: Use cap to puncture seal.

IMPORTANT: Do not use if seal has been punctured or is not visible. See crimp of tube for batch number and expiration date.

Manufactured and Distributed by:

Crown Laboratories, Inc.

Johnson City, TN 37604

Triderm (Triamcinolone Acetonide Cream USP), 0.025% carton label

NDC 0316-0165-15

Rx Only

TRIDERM CREAMTM

Triamcinolone Acetonide Cream USP, 0.025%

15 grams

WARNING: Keep out of reach of children

For External Use Only
Not for Ophthalmic Use

USUAL DOSAGE: 2 or 4 applications daily. See package insert for full prescribing information.

See end of carton for batch number and expiration date.

Each gram contains 0.25 mg triamcinolone acetonide USP in a cream base consisting of purified water, emulsifying wax, mineral oil, propylene glycol, sorbitol solution, cetyl palmitate, sorbic acid, and potassium sorbate.

Directions for puncturing seal: Remove cap. Turn cap upside down and place puncture tip onto tube seal; push down until seal is punctured. Screw cap back on to close

IMPORTANT: Do not use if seal has been punctured or is not visible.

Store at 20o-25oC (68o-77oF) [see USP Controlled Room Temperature]

Avoid excessive heat. Protect from freezing.

Manufactured and Distributed by: Crown Laboratories, Inc., Johnson City, TN 37604

Triderm (Triamcinolone Acetonide Cream USP), 0.5% tube label

NDC 0316-0175-15

Rx Only

TRIDERM CREAMTM

Triamcinolone Acetonide Cream USP, 0.5%

15 grams

WARNING: Keep out of reach of children

For External Use Only
Not for Ophthalmic Use

Store at 20o-25oC (68o-77oF) [see USP Controlled Room Temperature]

Avoid excessive heat. Protect from freezing.

Each gram contains 5 mg triamcinolone acetonide USP in a cream base consisting of purified water, emulsifying wax, mineral oil, propylene glycol, sorbitol solution, cetyl palmitate, sorbic acid, and potassium sorbate.

USUAL DOSAGE: 2 or 3 applications daily. See package insert for full prescribing information.

TO OPEN: Use cap to puncture seal.

IMPORTANT: Do not use if seal has been punctured or is not visible. See crimp of tube for batch number and expiration date.

Manufactured and Distributed by:

Crown Laboratories, Inc.

Johnson City, TN 37604

Triderm (Triamcinolone Acetonide Cream USP), 0.5% carton label

NDC 0316-0175-15

Rx Only

TRIDERM CREAMTM

Triamcinolone Acetonide Cream USP, 0.5%

15 grams

WARNING: Keep out of reach of children

For External Use Only
Not for Ophthalmic Use

USUAL DOSAGE: 2 or 3 applications daily. See package insert for full prescribing information.

See end of carton for batch number and expiration date.

Each gram contains 5 mg triamcinolone acetonide USP in a cream base consisting of purified water, emulsifying wax, mineral oil, propylene glycol, sorbitol solution, cetyl palmitate, sorbic acid, and potassium sorbate.

Directions for puncturing seal: Remove cap. Turn cap upside down and place puncture tip onto tube seal; push down until seal is punctured. Screw cap back on to close

IMPORTANT: Do not use if seal has been punctured or is not visible.

Store at 20o-25oC (68o-77oF) [see USP Controlled Room Temperature]

Avoid excessive heat. Protect from freezing.

Manufactured and Distributed by: Crown Laboratories, Inc., Johnson City, TN 37604